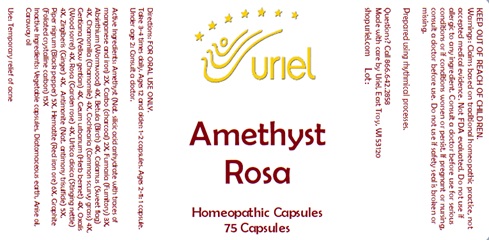 DRUG LABEL: Amethyst Rosa
NDC: 48951-1363 | Form: CAPSULE
Manufacturer: Uriel Pharmacy, Inc.
Category: homeopathic | Type: HUMAN OTC DRUG LABEL
Date: 20241209

ACTIVE INGREDIENTS: BETULA PUBESCENS BARK 4 [hp_X]/1 1; GINGER 4 [hp_X]/1 1; SILICON DIOXIDE 2 [hp_X]/1 1; URTICA DIOICA 4 [hp_X]/1 1; WORMWOOD 4 [hp_X]/1 1; BLACK PEPPER 5 [hp_X]/1 1; ACORUS CALAMUS ROOT 4 [hp_X]/1 1; COCHLEARIA OFFICINALIS FLOWERING TOP 4 [hp_X]/1 1; GENTIANA LUTEA ROOT 4 [hp_X]/1 1; ROSA RUGOSA FLOWER 4 [hp_X]/1 1; GEUM URBANUM ROOT 4 [hp_X]/1 1; SEDUM ROSEUM WHOLE 4 [hp_X]/1 1; GRAPHITE 15 [hp_X]/1 1; CHAMOMILE 4 [hp_X]/1 1; OXALIS STRICTA WHOLE 4 [hp_X]/1 1; ANTIMONY TRISULFIDE 5 [hp_X]/1 1; ACTIVATED CHARCOAL 2 [hp_X]/1 1; FUMARIA OFFICINALIS FLOWERING TOP 3 [hp_X]/1 1; FERRIC OXIDE RED 6 [hp_X]/1 1
INACTIVE INGREDIENTS: CARAWAY OIL; WATER; DIATOMACEOUS EARTH; ANISE OIL; POWDERED CELLULOSE

Amethyst Rosa

INDICATIONS AND USAGE

Directions: FOR ORAL USE ONLY.

DOSAGE AND ADMINISTRATION

Take 3-4 times daily. Ages 12 and older: 1-2 capsules. Ages 2-11: 1 capsule. Under age 2: Consult a doctor.

ACTIVE INGREDIENT

Active Ingredients: Amethyst (Nat. silicic acid anhydrate with traces of manganese and iron) 2X, Carbo (charcoal) 2X, Fumaria (Fumitory) 3X, Absinthium (Wormwood) 4X, Betula (Birch) 4X, Calamus (Sweet flag) 4X, Chamomilla (Chamomile) 4X, Cochlearia (Common scurvy grass) 4X, Gentiana (Yellow gentian) 4X, Geum urbanum (Herb bennet) 4X, Oxalis (Wood sorrel) 4X, Rosa (Garden rose) 4X, Urtica dioica (Stinging nettle) 4X, Zingiberis (Ginger) 4X, Antimonite (Nat. antimony trisulfide) 5x, Piper nigrum (Black pepper) 5X. Hematite (Red iron ore) 6X, Graphite (Foliated crystalline carbon) 15X,

INACTIVE INGREDIENT

Inactive Ingredients: Vegetable capsules, Diatomaceous earth, Distilled water, Anise oil, Caraway oil

Prepared using rhythmical processes.

PURPOSE

Use: Temporary relief of acne.

KEEP OUT OF REACH OF CHILDREN.

WARNINGS

Warnings: Claims based on traditional homeopathic practice, not accepted medical evidence. Not FDA evaluated. Do not use if allergic to any ingredient. Consult a doctor before use for serious conditions or if conditions worsen or persist. If pregnant or nursing, consult a doctor before use. Do not use if safety seal is broken or missing.

Questions? Call 866.642.2858
Made with care by Uriel, East Troy, WI 53120
shopuriel.com Lot: